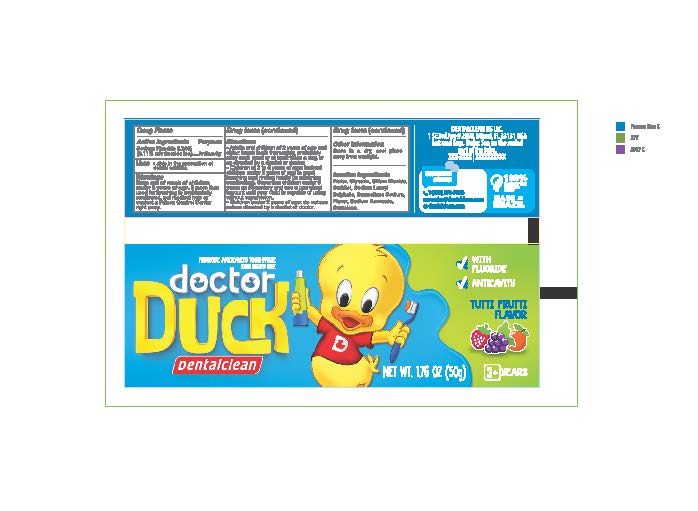 DRUG LABEL: Dentalclean Doctor Duck
NDC: 84035-008 | Form: PASTE, DENTIFRICE
Manufacturer: Rabbit Indústria e Comércio de Produtos de Higiene Pessoal Ltda
Category: otc | Type: HUMAN OTC DRUG LABEL
Date: 20240514

ACTIVE INGREDIENTS: SODIUM FLUORIDE 2.4 mg/1 g
INACTIVE INGREDIENTS: SUCRALOSE; SODIUM LAURYL SULFATE; WATER; SILICON DIOXIDE; SORBITOL; CARBOXYMETHYLCELLULOSE SODIUM, UNSPECIFIED FORM; GLYCEROL FORMAL; SODIUM BENZOATE

Dentalclean Doctor Duck

ACTIVE INGREDIENT

Sodium fluoride 0.24%

PURPOSE

Anticavity

INDICATIONS AND USAGE

Useaids in the prevention of dental cavities

WARNINGS

WARNINGS: If more than used for brushing is accidentally swallowed, get medical help or contact poison control center right away.

Directions

- Adults and children 2 years of age and older: brush teeth thoroughly, preferably after each meal or at least twice a day, or as directed by a dentist or doctor.

• Children 2 to 6 years of age: instruct children under 6 years of age in good brushing and rinsing habits (to minimize swallowing). Supervise children under 6 years as necessary and use a pea-sized amount until your child is capable of using without supervision.

• Children under 2 years of age: do not use unless directed by a dentist or doctor or as directed by a dentist or doctor.

OTHER SAFETY INFORMATION

Store in a dry, cool place away from sunlight.

Inactive Ingredients

Water, Glycerin, Silium Dioxide, Sorbitol, Sodium Lauryl Sulphate, Carmellose Sodium, Flavor, Sodium Benzoate, Sucralose

Keep out of reach of children under 6 years of age